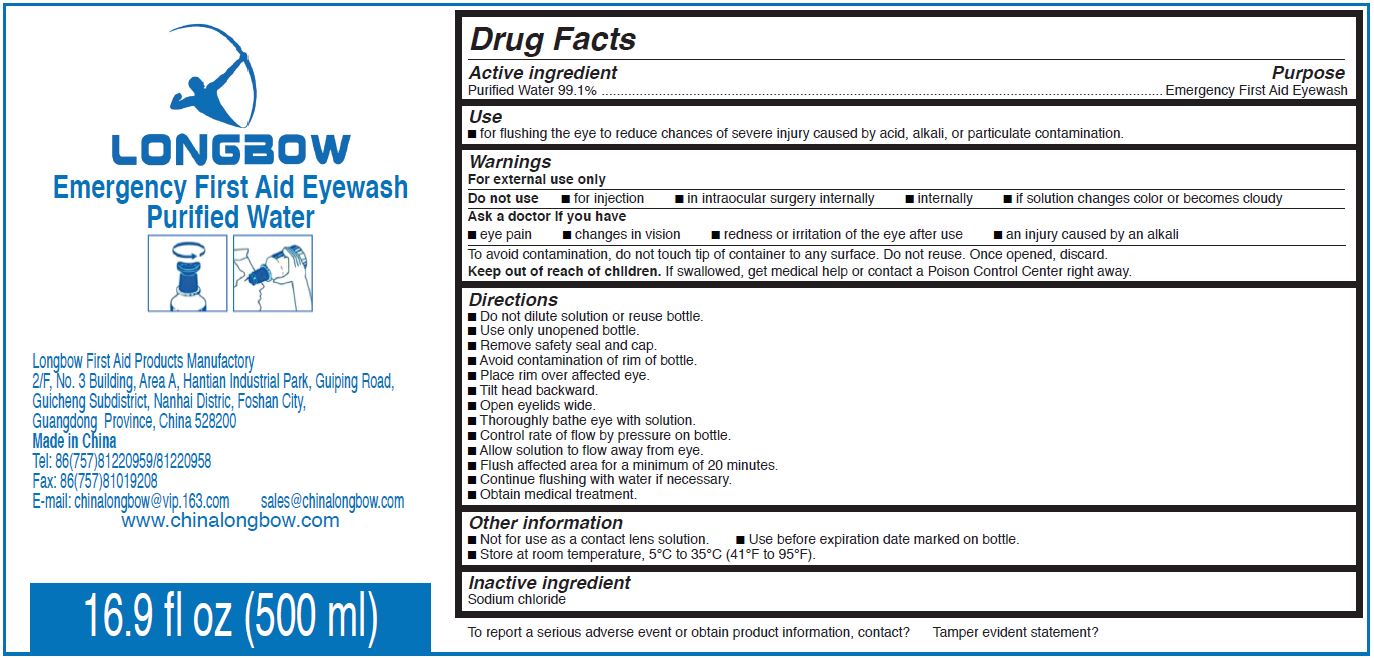 DRUG LABEL: Emergency First Aid Eyewash Purified Water
NDC: 70746-000 | Form: LIQUID
Manufacturer: Longbow first aid products manufactory
Category: otc | Type: HUMAN OTC DRUG LABEL
Date: 20160919

ACTIVE INGREDIENTS: WATER 0.991 mL/1 mL
INACTIVE INGREDIENTS: SODIUM CHLORIDE

Emergency First Aid Eyewash Purified Water

Active Ingredient

Purified Water 99.1 %

Purpose

Emergency First Aid Eyewash

Use

- For flushing the eye to reduce chances of severe injury caused by acid, alkali, or particulated contamination.

Warnings

For external use only.

Do not use

- for injection
- in intraocular surgery internally
- internally
- if solution changes color or becomes cloudy

Ask a doctor if you have

- eye pain
- cahnges in vision
- redness or irritation of the eye after use
- an injury caused by an alkili

To avoid contamination, do not touch the tip of container to any surface. Do not reuse. Once opened, discard.

Keep out of reach of children.

If swallowed, get medical help or contact Poison control Center right away.

Directions

- Do not dilute solution or reuse bottle.
- Use only unopened bottle.
- Remove safety seal and cap.
- Avoid contamination of rim of bottle.
- Place rim over affected eye.
- Tilt head backwards.
- Open eyelids wide.
- Throughtly bathe eye with solution.
- Control rate of flow by pressure on bottle.
- Allow solution to flow away from eye.
- Flush affected area for a minimum of 20 minutes.
- continue flushing with water if necessary.
- Obtain medical treatement.

Other information

- Not for use as a contact solution.
- use before expiration date market on bottle.
- Store at room temperature, 5^0C to 35^0C (41^0F to 95^0C).

Inactive ingredient

Sodium chloride